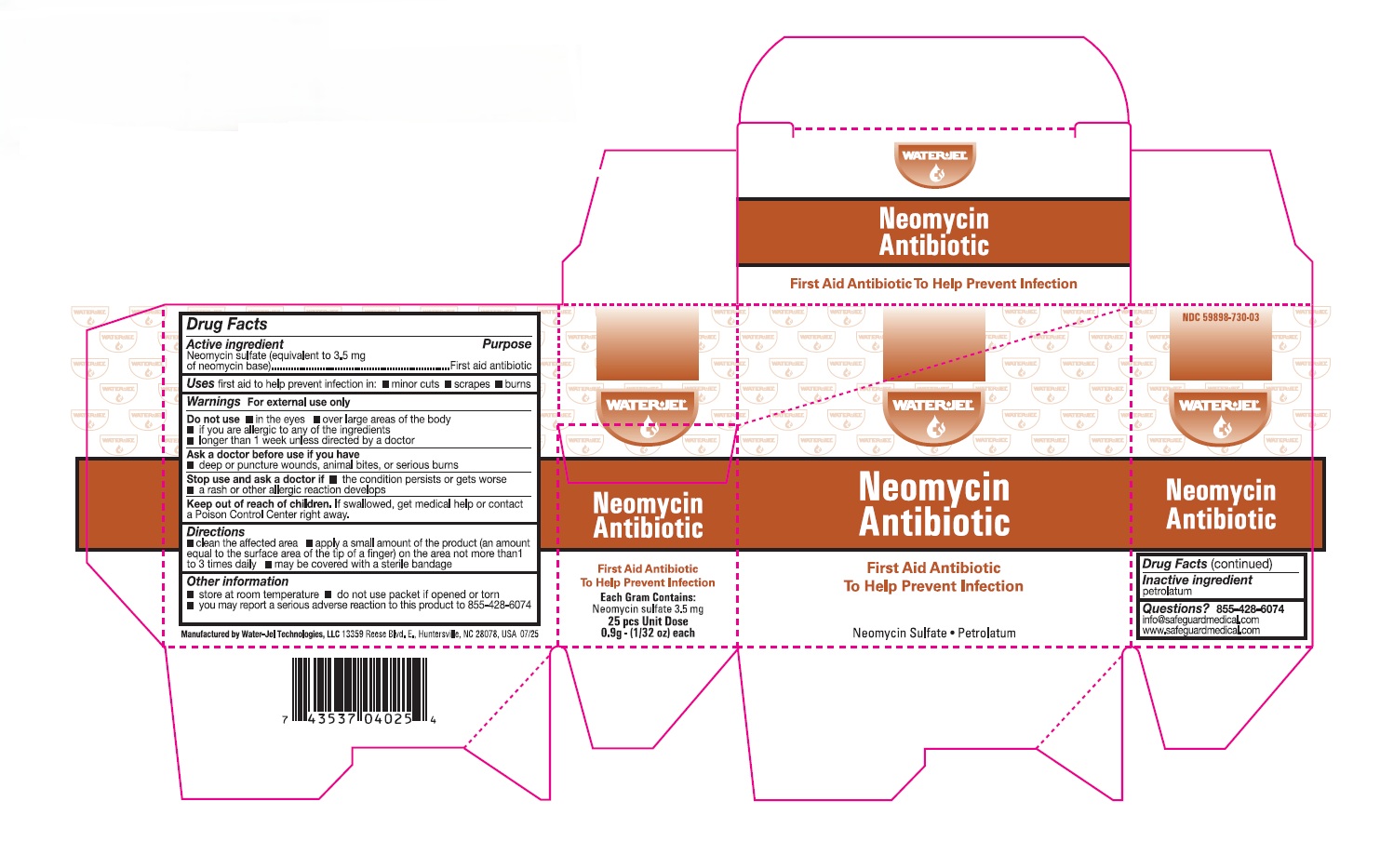 DRUG LABEL: Water-Jel Neomycin Antibiotic
NDC: 59898-730 | Form: OINTMENT
Manufacturer: Water-Jel Technologies
Category: otc | Type: HUMAN OTC DRUG LABEL
Date: 20251231

ACTIVE INGREDIENTS: NEOMYCIN SULFATE 3.5 mg/1 g
INACTIVE INGREDIENTS: PETROLATUM

Neomycin Antibiotic Ointment

Active Ingredient (Each gram contains)

Neomycin sulfate (5 mg equivalent to 3.5 mg Neomycin base)

Purpose

First aid antibiotic

Uses

first aid to help prevent infection in:

- minor cuts
- scrapes
- burns

Warnings

For external use only

Do not use

- in the eyes or over large areas of the body
- if you are allergic to any of the ingredients
- longer than 1 week unless directed by a doctor

Ask a doctor before use if you have

- a deep or puncture wounds, animal bites, or serious burns

Stop use and ask a doctor if

- the condition persists or gets worse
- a rash or other allergic reaction develops

Keep out of the reach of children

If swallowed, get medical help or contact a Poison Control Center right away.

Directions

- clean the affected area
- apply a small amount of the product (an amount equal to the surface area of the tip of a finger) on the area 1 to 3 times daily
- may be covered with a sterile bandage

Inactive ingredients

pertrolatum

Other information

- store at room temperature
- do not use packet if opened or torn
- you my report a serious adverse reaction o this product to 1-800-275-3433

Questions or comments?

1-855-428-6074

Manufactured by Water-Jel Technologies, LLC

13359 Reese Blvd E., Huntersville , NC 28078 USA